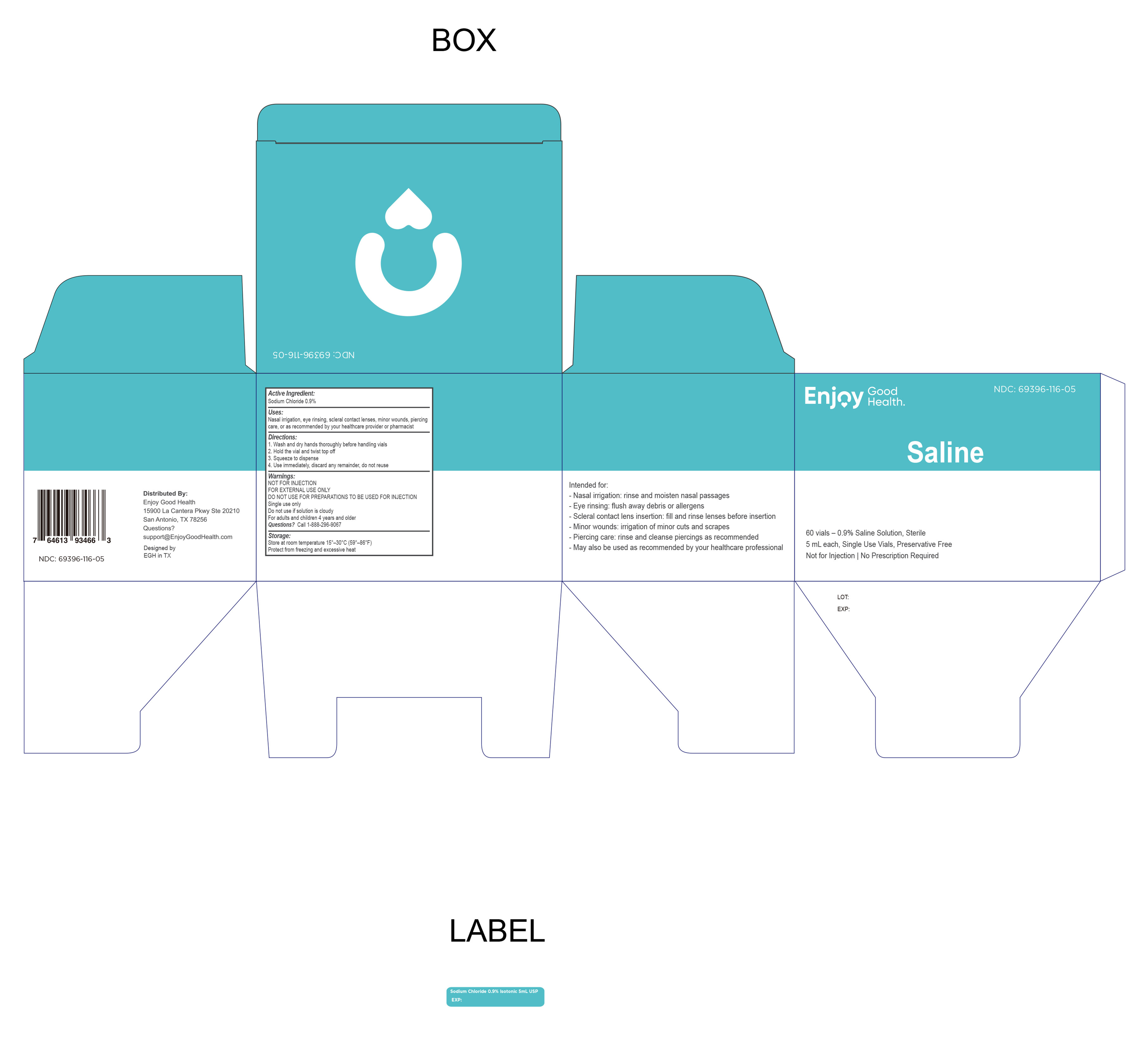 DRUG LABEL: Saline Ampoules
NDC: 69396-116 | Form: SPRAY
Manufacturer: Trifecta Pharmaceuticals USA, LLC.
Category: otc | Type: HUMAN OTC DRUG LABEL
Date: 20251013

ACTIVE INGREDIENTS: SODIUM CHLORIDE 9 mg/1 mL
INACTIVE INGREDIENTS: WATER

Enjoy Good Health
Pure and Sterile
0.9% Sodium Chloride Isotonic
5ml Single Use Saline Ampoules

Active Ingredient

Sodium Chloride 0.9%

Purpose

Moisturizer

INDICATIONS AND USAGE

This product may be used for conditions in the respiratory passages, nasal cavity or as directed by your healthcare provider.

Warnings

For External Use Only

Not for parenteral administration

When using this product a mild and temporary irritation may be experienced at the beginning of use.

Keep out of the reach of children

If swallowed, get medical help or contact a Poison Control Center right away.

If pregnant or breast feeding

Ask a doctor before use.

Do Not Use

- Same applicator on more than one individual
- If sensitive to any of the components

Directions

For Adults and children 4 years and older. Use as often as needed.

Children under 4 years of age consult a doctor.

Hold vial gently and twist top off

Squeeze vial to dispense

Discard after use

Other information

- Store at controlled room temperature 20º-25ºC (68º-77ºF) and protect from sunlight and sources of heat.
- See bottom of carton for Lot No. and Expiration data
- No Bacteriostatic or other preservatives added

Inactive Ingredients

Purified Water

Questions or Comments

Call 1-888-296-9067

Distributed By

Enjoy Good Health

15900 La Cantera Pkwy Ste 20210

San Antonio, TX 78256

Questions: support@enjoygoodhealth.com